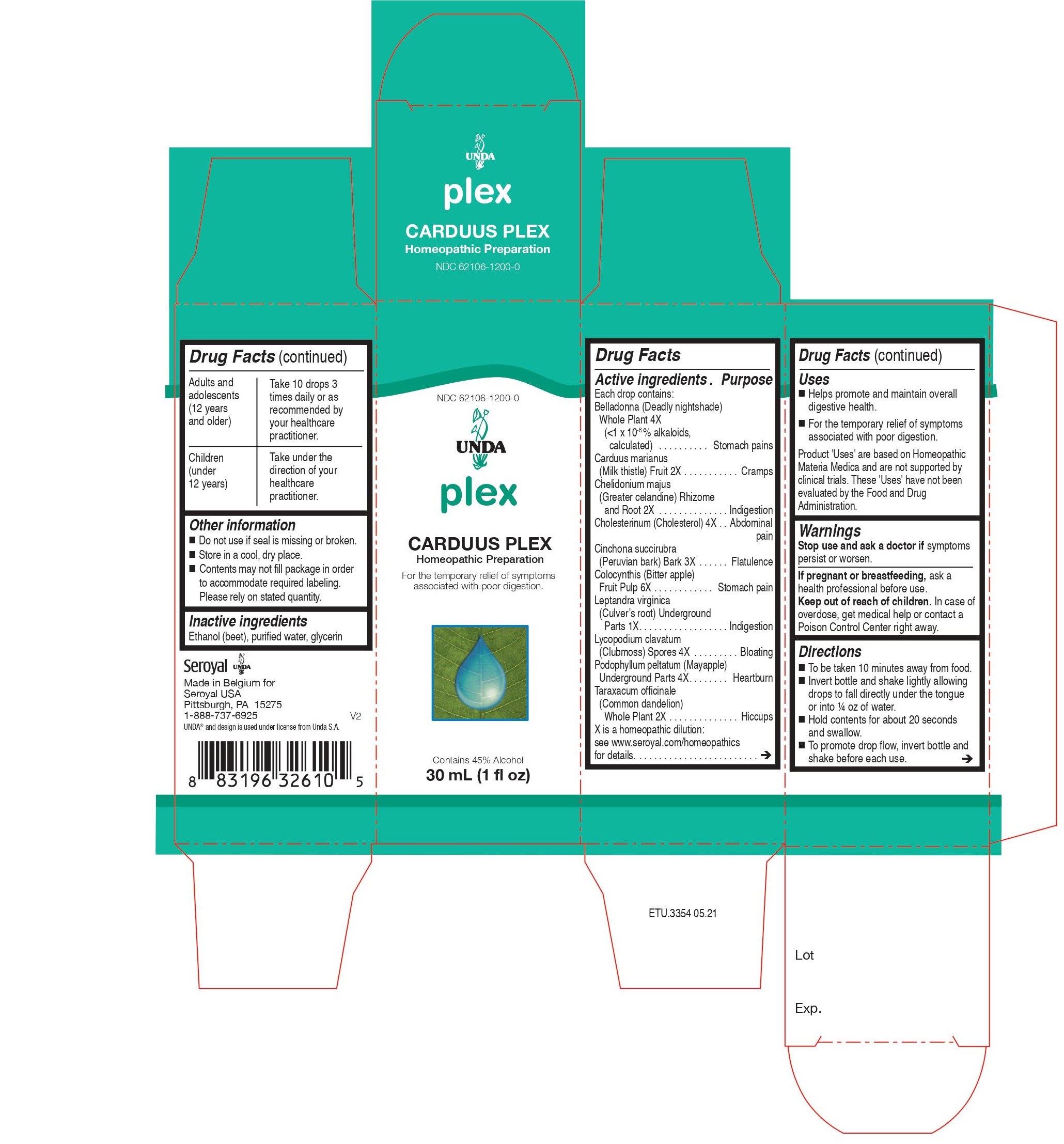 DRUG LABEL: CARDUUS PLEX
NDC: 62106-1200 | Form: LIQUID
Manufacturer: Seroyal USA
Category: homeopathic | Type: HUMAN OTC DRUG LABEL
Date: 20210714

ACTIVE INGREDIENTS: MILK THISTLE 2 [hp_X]/30 mL; CHOLESTEROL 4 [hp_X]/30 mL; LYCOPODIUM CLAVATUM SPORE 4 [hp_X]/30 mL; PODOPHYLLUM PELTATUM ROOT 4 [hp_X]/30 mL; TARAXACUM OFFICINALE 2 [hp_X]/30 mL; CHELIDONIUM MAJUS 2 [hp_X]/30 mL; CULVER'S ROOT 1 [hp_X]/30 mL; CITRULLUS COLOCYNTHIS FRUIT PULP 6 [hp_X]/30 mL; CINCHONA PUBESCENS BARK 3 [hp_X]/30 mL; ATROPA BELLADONNA 4 [hp_X]/30 mL
INACTIVE INGREDIENTS: ALCOHOL; WATER; GLYCERIN

CARDUUS PLEX

Active ingredients

Each drop contains:

Belladonna (Deadly nightshade) Whole Plant 4X (<1 x 10-6 % alkaloids, calculated)
Carduus marianus (Milk thistle) Fruit 2X
Chelidonium majus (Greater celandine) Rhizome and Root 2X
Cholesterinum (Cholesterol) 4X
Cinchona succirubra (Peruvian bark) Bark 3X
Colocynthis (Bitter apple) Fruit 6X
Leptandra virginica (Culver’s root) Underground Parts
Lycopodium clavatum (Clubmoss) Spores 4X
Podophyllum peltatum (Mayapple) Underground Parts 4X
Taraxacum officinale (Common dandelion)Whole Plant 2X

Uses
Helps promote and maintain overall digestive health.

For the temporary relief of symptoms associated with poor digestion.

Warnings
Stop use and ask a doctor if symptoms persist or worsen.
If pregnant or breastfeeding, ask a health professional before use.
Keep out of reach of children.

In case of overdose, get medical help or contact a Poison Control Center right away.

Keep out of reach of children.

In case of overdose, get medical help or contact a Poison Control Center right away.

PREGNANCY OR BREAST FEEDING

If pregnant or breastfeeding, ask a health professional before use.

Other information

- Do not use if seal is missing or broken.
- Store in a cool, dry place.
- Contents may not fill package in order to accommodate required labeling.Please rely on stated quantity.

Inactive ingredients
Ethanol (beet), glycerin, purified water

Directions
To be taken ten minutes away from food.
Invert bottle and shake lightly allowing drops to fall directly under the tongue or into ¼ oz of water.
Hold contents for about 20 seconds and swallow.
To promote drop flow, invert bottle and shake before each use.

Adults and adolescents (12 years and older)

Take 10 drops three times daily or as recommended by your healthcare practitioner.

Children (under 12 years)

Take under the direction of your healthcare practitioner.

Uses

Helps promote and maintain overall digestive health.
For the temporary relief of symptoms associated with poor digestion.

Directions
To be taken ten minutes away from food.
Invert bottle and shake lightly allowing drops to fall directly under the tongue or into ¼ oz of water.

Hold contents for about 20 seconds and swallow.
To promote drop flow, invert bottle and shake before each use.

Adults and adolescents (12 years and older)

Take 10 drops three times daily or as recommended by your healthcare practitioner.

Children (under 12 years)
Take under the direction of your healthcare practitioner.

PACKAGE LABEL

NDC 62106-1200-0

UNDA

plex

CARDUUS PLEX

Homeopathic Preparation

For the temporary relief of symptoms associated with poor digestion.

Contains 45% Alcohol
1 fl oz (30 mL)